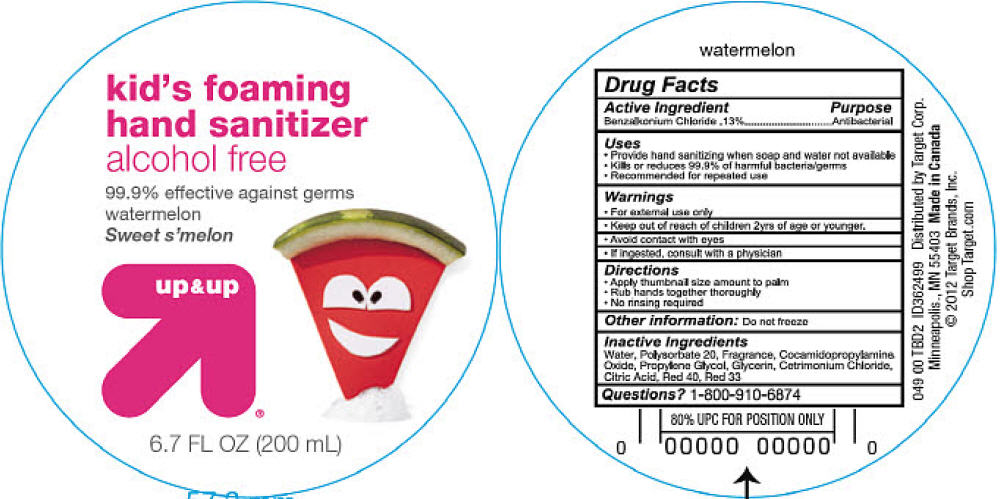 DRUG LABEL: Kids Foaming Hand Sanitizer Alcohol Free
NDC: 11673-811 | Form: LIQUID
Manufacturer: Target Brands
Category: otc | Type: HUMAN OTC DRUG LABEL
Date: 20120417

ACTIVE INGREDIENTS: Benzalkonium chloride 0.13 g/1 mL
INACTIVE INGREDIENTS: Water; Polysorbate 20; Cocamidopropylamine Oxide; Propylene Glycol; Glycerin; cetrimonium chloride; Citric Acid Monohydrate; FD&C Red No. 40; D&C Red No. 33

Kids Foaming Hand Sanitizer Alcohol Free

Drug Facts

Active Ingredient

Benzalkonium chloride .13%

Purpose

Antibacterial

Uses

- Provide hand sanitizing when soap and water not available
- Kills or reduces 99.9% of harmful bacteria/germs
- Recommended for repeated use

Warnings

- For external use only

- Keep out of reach of children 2 yrs of age or younger,

WHEN USING

- Avoid contact with eyes

ASK DOCTOR

- If ingested, consult with a physician

Directions

- Apply thumbnail size amount to palm
- Rub hands together thoroughly
- No rinsing required

Other Information

Do not freeze

Inactive ingredients

Water, Polysorbate 20, Fragrance, Cocamidopropylamine Oxide, Propylene Glycol, Glycerin, Cetrimonium Chloride, Citric Acid, Red 40, Red 43

Questions?

1-800-910-6874

Distributed by Target Corp.
Minneapolis., MN 55403

PRINCIPAL DISPLAY PANEL - 200 mL Bottle Label

kid's foaming
hand sanitizer
alcohol free

99.9% effective against germs
watermelon
Sweet s'melon

up&up®

6.7 FL OZ (200 mL)